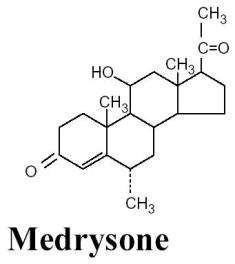 DRUG LABEL: Unknown
Manufacturer: Allergan, Inc.
Category: prescription | Type: HUMAN PRESCRIPTION DRUG LABELING
Date: 20060228

HMS®
(medrysone ophthalmic suspension) 1%

Sterile

DESCRIPTION

HMS® (medrysone ophthalmic suspension) 1% is a topical anti-inflammatory agent for ophthalmic use.

Chemical Name:

11β-hydroxy-6α-methylpregn-4-ene-3,20-dione

Structural Formula:

Contains: Active: Medrysone 1%. Preservative: benzalkonium chloride 0.004%.

Inactives: edetate disodium; hypromellose; polyvinyl alcohol 1.4%; potassium chloride; purified water; sodium chloride; sodium phosphate, dibasic; sodium phosphate, monobasic; and sodium hydroxide to adjust the pH (6.2 - 7.5).

CLINICAL PHARMACOLOGY

HMS® (medrysone ophthalmic suspension) is a synthetic corticosteroid with topical anti-inflammatory activity. Glucocorticoids inhibit the edema, fibrin deposition, capillary dilation and phagocytic migration of the acute inflammatory response as well as capillary proliferation, deposition of collagen, and scar formation. HMS® (medrysone ophthalmic suspension) has less anti-inflammatory potency than 0.1% dexamethasone.

INDICATIONS AND USAGE

HMS® (medrysone ophthalmic suspension) is indicated for the treatment of allergic conjunctivitis, vernal conjunctivitis, episcleritis, and epinephrine sensitivity.

CONTRAINDICATIONS

HMS® suspension is contraindicated in most viral diseases of the cornea and conjunctiva, including epithelial herpes simplex keratitis (dendritic keratitis), vaccinia, and varicella, and also in mycobacterial infection of the eye and fungal diseases of ocular structures. HMS® suspension is also contraindicated in individuals with known or suspected hypersensitivity to any of the ingredients of this preparation and to other corticosteroids.

WARNINGS

HMS® (medrysone ophthalmic suspension) is not recommended for use in iritis and uveitis as its therapeutic effectiveness has not been demonstrated in these conditions.

Prolonged use of corticosteroids may result in glaucoma with damage to the optic nerve, defects in visual acuity and fields of vision, and in posterior subcapsular cataract formation. Prolonged use may also suppress the host immune response and thus increase the hazard of secondary ocular infections.

Various ocular diseases and long-term use of topical corticosteroids have been known to cause corneal and scleral thinning. Use of topical corticosteroids in the presence of thin corneal or scleral tissue may lead to perforation.

Acute purulent infections of the eye may be masked or activity enhanced by the presence of corticosteroid medication.

If this product is used for 10 days or longer, intraocular pressure should be routinely monitored even though it may be difficult in children and uncooperative patients.

Steroids should be used with caution in the presence of glaucoma. Intraocular pressure should be checked frequently.

The use of steroids after cataract surgery may delay healing and increase the incidence of bleb formation.

Use of ocular steroids may prolong the course and may exacerbate the severity of many viral infections of the eye (including herpes simplex). Employment of a corticosteroid medication in the treatment of patients with a history of herpes simplex requires great caution; frequent slit lamp microscopy is recommended.

Corticosteroids are not effective in mustard gas keratitis and Sjögren's keratoconjunctivitis.

PRECAUTIONS

General:

The initial prescription and renewal of the medication order beyond 20 milliliters of HMS® suspension should be made by a physician only after examination of the patient with the aid of magnification, such as slit lamp biomicroscopy and, where appropriate, fluorescein staining. If signs and symptoms fail to improve after two days, the patient should be re-evaluated.

As fungal infections of the cornea are particularly prone to develop coincidentally with long-term local corticosteroid applications, fungal invasion should be suspected in any persistent corneal ulceration where a corticosteroid has been used or is in use. Fungal cultures should be taken when appropriate.

If this product is used for 10 days or longer, intraocular pressure should be monitored (see WARNINGS).

Information for Patients:

If inflammation or pain persists longer than 48 hours or becomes aggravated, the patient should be advised to discontinue use of the medication and consult a physician.

This product is sterile when packaged. To prevent contamination, care should be taken to avoid touching the bottle tip to eyelids or to any other surface. The use of this bottle by more than one person may spread infection. Keep bottle tightly closed when not in use. Keep out of the reach of children.

Carcinogenesis, Mutagenesis, Impairment of Fertility:

No studies have been conducted in animals or in humans to evaluate the potential of these effects.

Pregnancy:

TERATOGENIC EFFECTS

Teratogenic effects. Pregnancy Category C. Medrysone has been shown to be embryocidal in rabbits when given in doses 10 and 30 times the human ocular dose. Two drops of medrysone were applied to both eyes of pregnant rabbits 4 times per day on day 6 through 18 of gestation. A significant increase in early resorptions was observed in the treated rabbits. There are no adequate and well-controlled studies of medrysone in pregnant women. Medrysone should be used during pregnancy only if the potential benefit justifies the potential risk to the fetus.

Nursing Mothers:

It is not known whether topical ophthalmic administration of corticosteroids could result in sufficient systemic absorption to produce detectable quantities in human breast milk. Systemically administered corticosteroids appear in human milk and could suppress growth, interfere with endogenous corticosteroid production, or cause other untoward effects. Because of the potential for serious adverse reactions in nursing infants from medrysone, a decision should be made whether to discontinue nursing or to discontinue the drug, taking into account the importance of the drug to the mother.

Pediatric Use:

Safety and effectiveness in pediatric patients below the age of 3 years have not been established.

Geriatric Use:

No overall differences in safety or effectiveness have been observed between elderly and younger patients.

ADVERSE REACTIONS

Adverse reactions include, in decreasing order of frequency, elevation of intraocular pressure (IOP) with possible development of glaucoma and infrequent optic nerve damage, posterior subcapsular cataract formation, and delayed wound healing.

Although systemic effects are extremely uncommon, there have been rare occurrences of systemic hypercorticoidism after use of topical steroids.

Corticosteroid-containing preparations have also been reported to cause acute anterior uveitis and perforation of the globe. Keratitis, conjunctivitis, corneal ulcers, mydriasis, conjunctival hyperemia, loss of accommodation and ptosis have occasionally been reported following local use of corticosteroids.

The development of secondary ocular infection (bacterial, fungal and viral) has occurred. Fungal and viral infections of the cornea are particularly prone to develop coincidentally with long-term applications of steroids. The possibility of fungal invasion should be considered in any persistent corneal ulceration where steroid treatment has been used (see WARNINGS).

Transient burning and stinging upon instillation and other minor symptoms of ocular irritation have been reported with the use of HMS® suspension. Other adverse events reported with the use of HMS® suspension include: allergic reactions, foreign body sensation, and visual disturbance (blurry vision).

OVERDOSAGE

Overdosage will not ordinarily cause acute problems. If accidentally ingested, drink fluids to dilute.

DOSAGE AND ADMINISTRATION

Shake well before using. Instill one drop into the conjunctival sac up to every four hours.

HOW SUPPLIED

HMS® (medrysone ophthalmic suspension) 1% is supplied sterile in opaque white LDPE plastic bottles with droppers with white high impact polystyrene (HIPS) caps as follows:

5 mL in 10 mL bottle - | NDC 11980-074-05
10 mL in 15 mL bottle - | NDC 11980-074-10

Note: Store at temperatures up to 25°C (77°F). Protect from freezing.

Rx Only

Revised August 2004

© 2004 Allergan, Inc.
Irvine, CA 92612, U.S.A.
6089X

® Marks owned by Allergan, Inc.
71741US11P